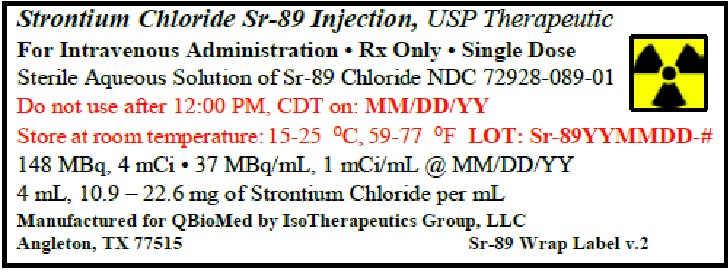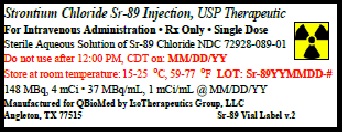 DRUG LABEL: STRONTIUM CHLORIDE Sr-89
NDC: 72928-089 | Form: INJECTION
Manufacturer: Q BioMed Inc
Category: prescription | Type: HUMAN PRESCRIPTION DRUG LABEL
Date: 20221019

ACTIVE INGREDIENTS: STRONTIUM CHLORIDE SR-89 1 mCi/1 mL
INACTIVE INGREDIENTS: water

THERAPEUTIC
For Intravenous Administration • Rx Only • Single Dose

DESCRIPTION

STRONTIUM CHLORIDE Sr-89 INJECTION, USP is a sterile, non-pyrogenic, aqueous solution of Strontium-89 Chloride for intravenous administration. The solution contains no preservative. Each milliliter contains:

Strontium Chloride 10.9 - 22.6 mg
Water for Injection q.s. to 1 mL

The radioactive concentration is 37 MBq/mL, 1 mCi/mL, and the specific activity is 2.96-6.17 MBq/mg, 80-167 µCi/mg at calibration. The pH of the solution is 4 - 7.5.

PHYSICAL CHARACTERISTIC

Strontium-89 decays by beta emission with a physical half-life of 50.5 days. The maximum beta energy is 1.463 MeV (100%). The maximum range of ß- particles from Strontium-89 in tissue is approximately 8 mm.

Radioactive decay factors to be applied to the stated value for radioactive concentration at calibration, when calculating injection volumes at the time of administration, are given in Table 1.

Table 1: Decay of Strontium-89

Day* | Factor | Day* | Factor
-24 | 1.39 | +6 | 0.92
-22 | 1.35 | +8 | 0.90
-20 | 1.32 | +10 | 0.87
-18 | 1.28 | +12 | 0.85
-16 | 1.25 | +14 | 0.83
-14 | 1.21 | +16 | 0.80
-12 | 1.18 | +18 | 0.78
-10 | 1.15 | +20 | 0.76
-8 | 1.12 | +22 | 0.74
-6 | 1.09 | +24 | 0.72
-4 | 1.06 | +26 | 0.70
-2 | 1.03 | +28 | 0.68
0=calibration | 1.00

* Days before (-) or after (+) the calibration date stated on the vial.

CLINICAL PHARMACOLOGY

Following intravenous injection, soluble strontium compounds behave like their calcium analogs, clearing rapidly from the blood and selectively localizing in bone mineral. Uptake of strontium by bone occurs preferentially in sites of active osteogenesis; thus primary bone tumors and areas of metastatic involvement (blastic lesions) can accumulate significantly greater concentrations of strontium than surrounding normal bone.

Strontium-89 Chloride is retained in metastatic bone lesions much longer than in normal bone, where turnover is about 14 days. In patients with extensive skeletal metastases, well over half of the injected dose is retained in the bones.

Excretion pathways are two-thirds urinary and one-third fecal in patients with bone metastases. Urinary excretion is higher in people without bone lesions. Urinary excretion is greatest in the first two days following injection.

Strontium-89 is a pure beta emitter and Strontium-89 Chloride selectively irradiates sites of primary and metastatic bone involvement with minimal irradiation of soft tissues distant from the bone lesions. (The maximum range in tissue is 8 mm; maximum energy is 1.463 MeV.) Mean absorbed radiation doses are listed under the Radiation Dosimetry section.

Clinical trials have examined relief of pain in cancer patients who have received therapy for bone metastases (external radiation to indexed sites) but in whom persistent pain recurred. In a multi-center Canadian placebo-controlled trial of 126 patients, pain relief occurred in more patients treated with a single injection of Strontium-89 Chloride than in patients treated with an injection of placebo. Results are given in the following tables.

Table 2 compares the percentage and number of patients treated with Strontium-89 Chloride Injection or placebo who had reduced pain and no increase in analgesic or radiotherapy re-treatment.

Table 2: Comparison of the effects of Strontium-89 and placebo, as adjunct to radiotherapy, on treatment outcome over time.

Months Post-Treatment

 | 1 | 2 | 3 | 4 | 5 | 6
Strontium-89 | 71.4% | 78.9% | 60.6% | 59.3% | 36.4% | 63.6%
 | (n=42) | (n=38) | (n=33) | (n=27) | (n=22) | (n=22)
Placebo | 61.4% | 57.1% | 55.9% | 25.0% | 31.8% | 35.0%
 | (n=44) | (n=35) | (n=34) | (n=24) | (n=22) | (n=20)

At each visit, treatment success, defined as a reduction in a patient’s pain score without any increase in analgesic intake and without any supplementary radiotherapy at the index site, was more frequent among patients assigned to Strontium-89 Chloride Injection than to placebo.

Table 3 compares the number and percentage of patients treated with Strontium-89 Chloride Injection or placebo as an adjunct to radiotherapy who were pain free without analgesic at the intervals shown.

Table 3: Comparison of the effects of Strontium-89 and placebo, as adjunct to radiotherapy, on reduction of pain score and analgesic score to zero.

Months Post-Treatment

 | 1 | 2 | 3 | 4 | 5 | 6 | 9
Strontium-89 | 6 | 5 | 5 | 3 | 4 | 4 | 2
 | 14.3% | 13.2% | 15.2% | 11.1% | 18.2% | 18.2% | 18.2%
 | (n=42) | (n=38) | (n=33) | (n=27) | (n=22) | (n=22) | (n=11)
Placebo | 3 | 3 | 2 | 0 | 1 | 1 | 0
 | 6.8% | 8.6% | 5.9% |  | 4.5% | 5%
 | (n=44) | (n=35) | (n=34) | (n=32) | (n=22) | (n=20) | (n=17)

The number of patients classified at each visit as treatment successes who were pain free at the index site and required no analgesics was consistently higher in the Strontium-89 group.

New pain sites were less frequent in patients treated with Strontium-89.

In another clinical trial, pain relief was greater in a group of patients treated with Strontium-89 compared with a group treated with non-radioactive Strontium-88.

INDICATIONS AND USAGE

STRONTIUM CHLORIDE Sr-89 INJECTION, USP is indicated for the relief of bone pain in patients with painful skeletal metastases.

The presence of bone metastases should be confirmed prior to therapy.

CONTRAINDICATIONS

None known.

WARNINGS

Use of Strontium-89 Chloride Injection in patients with evidence of seriously compromised bone marrow from previous therapy or disease infiltration is not recommended unless the potential benefit of the treatment outweighs its risks. Bone marrow toxicity is to be expected following the administration of Strontium-89, particularly white blood cells and platelets. The extent of toxicity is variable. It is recommended that the patient’s peripheral blood cell counts be monitored at least once every other week. Typically, platelets will be depressed by about 30% compared to pre-administration levels. The nadir of platelet depression in most patients is found between 12 and 16 weeks following administration of Strontium-89 Chloride Injection. White blood cells are usually depressed to a varying extent compared to pre-administration levels. Thereafter, recovery occurs slowly, typically reaching pre-administration levels six months after treatment unless the patient's disease or additional therapy intervenes.

In considering repeat administration of Strontium-89 Chloride Injection, the patient’s hematologic response to the initial dose, current platelet level and other evidence of marrow depletion should be carefully evaluated.

Verification of dose and patient identification is necessary prior to administration because Strontium-89 delivers a relatively high dose of radioactivity.

Strontium-89 Chloride Injection may cause fetal harm when administered to a pregnant woman. There are no adequate and well-controlled studies in pregnant women. If this drug is used during pregnancy, or if the patient becomes pregnant while receiving this drug, the patient should be apprised of the potential hazard to the fetus. Women of childbearing potential should be advised to avoid becoming pregnant.

PRECAUTIONS

Strontium-89 Chloride Injection is not indicated for use in patients with cancer not involving bone. Strontium-89 Chloride Injection should be used with caution in patients with platelet counts below 60,000 and white cell counts below 2,400.

Radiopharmaceuticals should only be used by physicians who are qualified by training and experience in the safe use and handling of radionuclides and whose experience and training have been approved by the appropriate government agency authorized to license the use of radionuclides.

STRONTIUM CHLORIDE Sr-89 INJECTION, USP like other radioactive drugs, must be handled with care and appropriate safety measures taken to minimize radiation to clinical personnel.

In view of the delayed onset of pain relief, typically 7 to 20 days post injection; administration of Strontium-89 Chloride Injection to patients with very short life expectancy is not recommended.

A calcium-like flushing sensation has been observed in patients following a rapid (less than 30 second injection) administration.

Special precautions, such as urinary catheterization, should be taken following administration to patients who are incontinent to minimize the risk of radioactive contamination of clothing, bed linen and the patient’s environment.

Strontium-89 Chloride is excreted primarily by the kidneys. In patients with renal dysfunction, the possible risks of administering Strontium-89 Chloride Injection should be weighed against the possible benefits.

Carcinogenesis, Mutagenesis, Impairment of Fertility

Data from a repetitive dose animal study suggests that Strontium-89 Chloride is a potential carcinogen. Thirty-three of 40 rats injected with Strontium-89 Chloride in ten consecutive monthly doses of either 250 or 350 µCi/kg developed malignant bone tumors after a latency period of approximately 9 months. No neoplasia was observed in the control animals. Treatment with Strontium-89 Chloride should be restricted to patients with well documented metastatic bone disease.

Adequate studies with Strontium-89 Chloride have not been performed to evaluate mutagenic potential or effects on fertility.

Pregnancy: Teratogenic effects.

Pregnancy Category D. See Warnings section.

Nursing Mothers

Because Strontium acts as a calcium analog, secretion of Strontium-89 Chloride into human milk is likely. It is recommended that nursing be discontinued by mothers about to receive intravenous Strontium-89 Chloride. It is not known whether this drug is excreted in human milk.

Pediatric Use

Safety and effectiveness in children below the age of 18 years have not been established.

ADVERSE REACTIONS

A single case of fatal septicemia following leukopenia was reported during clinical trials. Most severe reactions of marrow toxicity can be managed by conventional means.

A small number of patients have reported a transient increase in bone pain at 36 to 72 hours after injection. This is usually mild and self-limiting, and controllable with analgesics. A single patient reported chills and fever 12 hours after injection without long-term sequelae.

Additional post-marketing reactions include the following: hot flush.

DOSAGE AND ADMINISTRATION

The recommended dose of Strontium-89 Chloride is 148 MBq, 4 mCi, administered by slow intravenous injection (1-2 minutes). Alternatively, a dose of 1.5 - 2.2 MBq/kg, 40-60 µCi/kg body weight may be used.

Repeated administrations of Strontium-89 Chloride should be based on an individual patient’s response to therapy, current symptoms, and hematologic status, and are generally not recommended at intervals of less than 90 days.

The patient dose should be measured by a suitable radioactivity calibration system immediately prior to administration.

RADIATION DOSIMETRY

The estimated radiation dose that would be delivered over time by the intravenous injection of 37 MBq, 1 mCi of Strontium-89 to a normal healthy adult is given in Table 4. Data are taken from the ICRP publication “Radiation Dose to Patients from Radiopharmaceuticals”-ICRP #53, Vol. 18, No. 1-4, Page 171, Pergamon Press, 1988.

Table 4: Strontium-89 Dosimetry

Organ | mGy/MBq | rad/mCi
Bone Surface | 17.0 | 63.0
Red Bone Marrow | 11.0 | 40.7
Lower Bowel Wall | 4.7 | 17.4
Bladder Wall | 1.3 | 4.8
Testes | 0.8 | 2.9
Ovaries | 0.8 | 2.9
Uterine Wall | 0.8 | 2.9
Kidneys | 0.8 | 2.9

When blastic osseous metastases are present, significantly enhanced localization of the radiopharmaceutical will occur with correspondingly higher doses to the metastases compared with normal bones and other organs.

The radiation dose hazard in handling Strontium-89 Chloride injection during dose dispensing and administration is similar to that from phosphorus-32. The beta emission has a range in water of about 8 mm (max.) and in glass of about 3 mm, but the bremsstrahlung radiation may augment the contact dose.

Measured values of the dose on the surface of the unshielded vial are about 65 mR/minute/mCi.

It is recommended that the vial be kept inside its transportation shield whenever possible.

HOW SUPPLIED/STORAGE AND HANDLING

STRONTIUM CHLORIDE Sr-89 INJECTION, USP is supplied in a 5 mL vial containing 148 MBq, 4 mCi. The vial is shipped in a transportation shield-container with a package insert, and two therapeutic agent-warning labels.

The vial and its contents should be stored inside its transportation container at room temperature (15-25°C, 59-77°F).

The calibration date and expiration date are quoted on the vial label. Do not use after the expiration date. Stability studies have shown no change in any of the product characteristics monitored during routine product quality control over the period from manufacture to expiration.

This radiopharmaceutical is licensed by the Texas Department of Health, or under equivalent licesnses of the U.S. Nuclear Regulatory Comminssion or an agreement state.

NDC72928-089-01

PRODUCT INFORMATION ISSUED: January 20, 2020

Manufactured for:
Q BioMed, Inc.
366 Madison Ave, Third Floor
New York, NY 10017

Manufactured by:
Isotherapeutics Group LLC
1004 S. Velasco St.
Angleton, Texas (TX) 77515

Printed in U.S.A.
L-089-11I
Product Code: P089-0

Drug Product Label

Vial Label

Outer Container Label